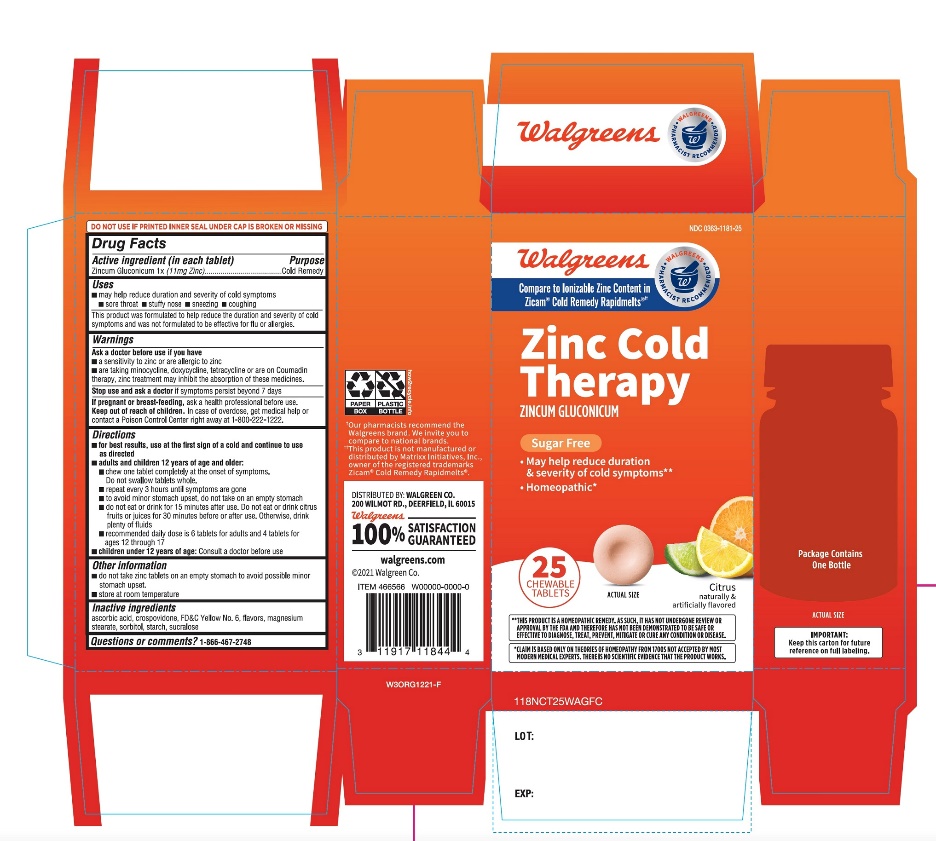 DRUG LABEL: Walgreen Zinc Cold Therapy

NDC: 0363-1181 | Form: TABLET, CHEWABLE
Manufacturer: WALGREENS CO.
Category: homeopathic | Type: HUMAN OTC DRUG LABEL
Date: 20251125

ACTIVE INGREDIENTS: ZINC GLUCONATE 1 [hp_X]/1 1
INACTIVE INGREDIENTS: ASCORBIC ACID; CROSPOVIDONE (120 .MU.M); FD&C YELLOW NO. 6; MAGNESIUM STEARATE; SORBITOL; STARCH, CORN; SUCRALOSE

Walgreen Cold Therapy Citrus Flavor 25 Chewable Tablets

Drug Facts

Active Ingredient (in each tablet)

Zincum Gluconicum 1x (11mg Zinc)

Purpose

Cold Remedy

Uses

- may help reduce duration and severity of cold symptoms
  - sore throat
  - stuffy nose
  - sneezing
  - coughing
- This product was formulated to help reduce the duration and severity of cold symptoms and was not formulated to be effective for flu or allergies.

Warnings

Ask a doctor before use if you have

- a sensitivity to zinc or are allergic zinc
- are taking minocycline, doxycycline, tetracycline or are on Coumadin therapy, zinc treatment may inhibit the absorption of these medicines.

Stop Use and ask a doctor

If symptoms persist beyond 7 days.

If pregnant or breast feeding

ask a health professional before use.

Keep Out of reach of children

In case of overdose, get medical help or contact a Poison Control Center right away at 1-800-222-1222.

Directions

- for best results, use at the first sign of a cold and continue to use as directed
- adults and children 12 years of age and older:
- chew one tablet at the onset of symptoms
- repeat every 3 hours until symptoms are gone
- to avoid minor stomach upset, do not take on an empty stomach.
- do not eat or drink for 15 minutes after use. Do not eat or drink citrus fruits or juices for 30 minutes before or after use. Otherwise, drink plenty of fluids.
- recommended daily dose is 6 tablets for adults and 4 tablets for ages 12 through 17
- Children under 12 years of age:Consult a doctor before use.

Other information

- do not take zinc tablets on an empty stomach to avoid possible minor stomach upset.
- store at room temperature

Inactive ingredients

ascorbic acid, crospovidone, FD&C yellow # 6 lake, magnesium stearate, natural and artificial flavor, sorbitol, starch, sucralose.

Questions or comments?

1-866-467-2748

PRINCIPAL DISPLAY PANEL

Walgreens

NDC 0363-1181-25

Compare to Ionizable Zinc Content in Zicam®Cold Remedy Rapid Melts®††

Zinc

Cold Therapy

ZINCUM GLUCONICUM

- May help reduce duration and severity of cold symptoms**
- Sugar free
- Homeopathic**

CITRUS FLAVOR

Naturally and Artificially Flavored

25CHEWABLE TABLETS

DO NOT USE IF PRINTED INNER SEAL UNDER CAP IS BROKEN OR MISSING.

**THIS PRODUCT IS A HOMEOPATHIC REMEDY, AS SUCH, IT HAS NOT UNDERGONE REVIEW ON APPROVAL BY THE FDA AND THEREFORE HAS NOT BEEN DEMONSTRATED TO BE SAFE OR EFFECTIVE TO DIAGNOSE, TREAT, PREVENT, MITIGATE OR CURE ANY CONDITION OR DISEASE.

IMPORTANT: Keep this carton for future reference on full labeling.

Gluten Free

††This product is not manufactured or distributed by Matrixx LLC, the distributor Zicam®Rapidmelts®

DISTRIBUTED BY: WALGREEN CO.

200 WILMOT RD., DEERFIELD, IL 60015

Walgreens ©2017 Walgreen Co.

100% SATISFACTION GUARANTEED